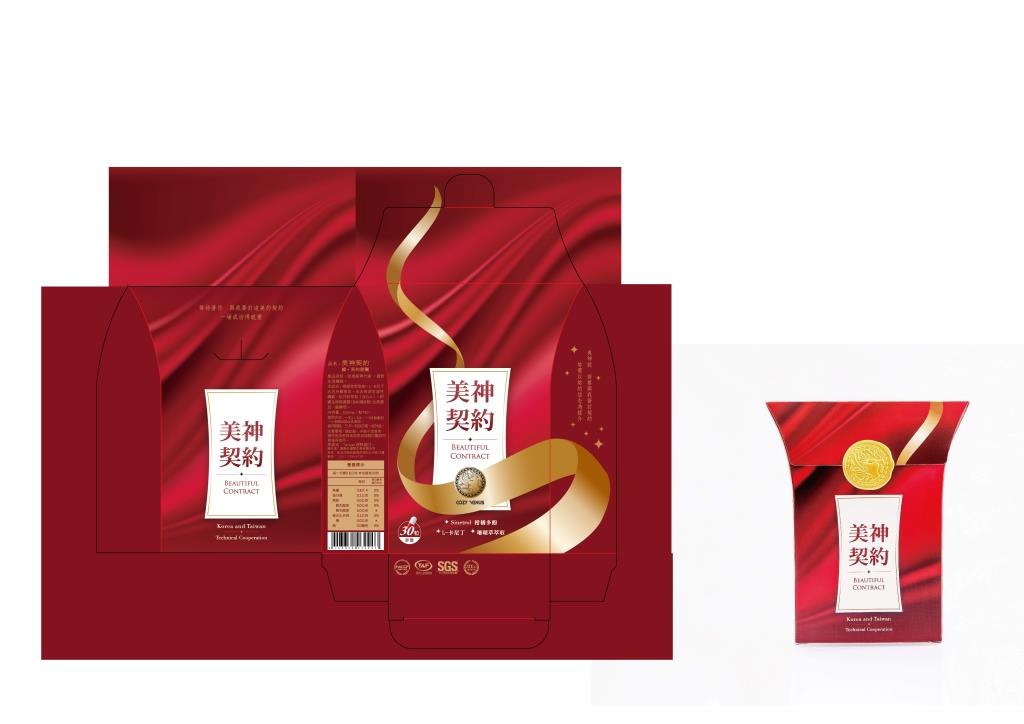 DRUG LABEL: BEAUTIFUL CONTRACT - Slimming contract
NDC: 70470-9951 | Form: CAPSULE, GELATIN COATED
Manufacturer: Phytopia Co., Ltd.
Category: homeopathic | Type: HUMAN OTC DRUG LABEL
Date: 20170201

ACTIVE INGREDIENTS: LEVOCARNITINE 210 mg/600 mg; LECITHIN, SOYBEAN 36 mg/600 mg
INACTIVE INGREDIENTS: MALTODEXTRIN; SAFFLOWER OIL; CITRUS BIOFLAVONOIDS; PHASEOLUS VULGARIS WHOLE; YEAST; CARRAGEENAN

Drug Facts

Levocarnitine 210mg

Soybean Lecithin 36mg

Use

For treatment of bulimia, obesity and help of weight control.

Dosage Suggestion

2 capsules maximum per day

INACTIVE INGREDIENT

Other Ingredients

Carrageenan, Maltodextrin, Safflower Oil, Citrus bioflavonoids, Phaseolus vulgaris, Yeast.

Directions

Take one capsule 60 minutes before meal, and drink at least 500ml water.

Warnings

For external use only. Stop use and ask doctor if rash occurs. Keep out reach of children.

Other Information

Protect this product from excessive heat

and direct sun.

Warnings

For external use only. Stop use and ask doctor if rash occurs. Keep out reach of children.